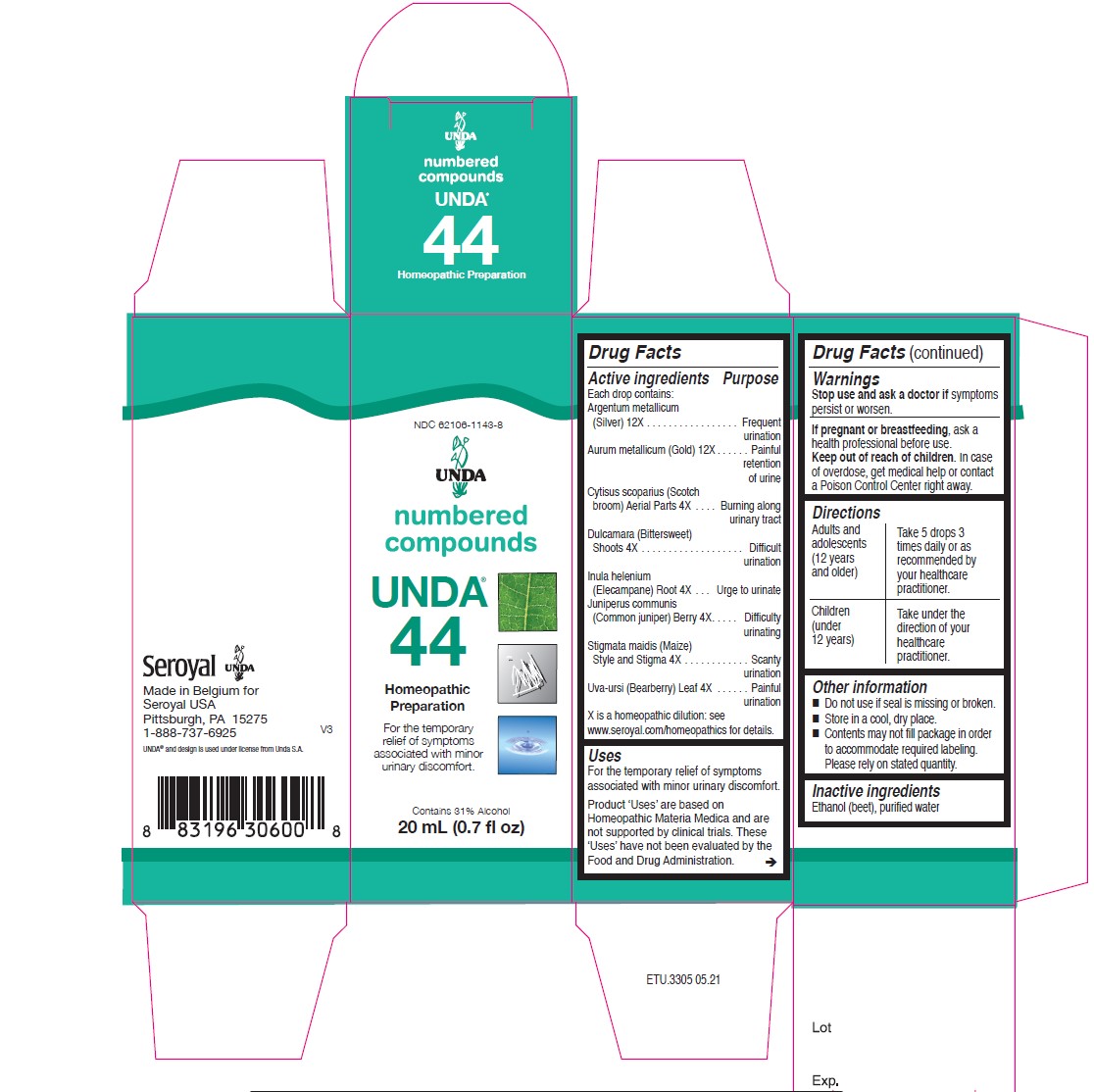 DRUG LABEL: Unda 44
NDC: 62106-1143 | Form: LIQUID
Manufacturer: Seroyal USA
Category: homeopathic | Type: HUMAN OTC DRUG LABEL
Date: 20220707

ACTIVE INGREDIENTS: GOLD 12 [hp_X]/20 mL; SILVER 12 [hp_X]/20 mL; JUNIPER BERRY 4 [hp_X]/20 mL; ARCTOSTAPHYLOS UVA-URSI LEAF 4 [hp_X]/20 mL; SOLANUM DULCAMARA STEM 4 [hp_X]/20 mL; CYTISUS SCOPARIUS FLOWERING TOP 4 [hp_X]/20 mL; CORN SILK 4 [hp_X]/20 mL; INULA HELENIUM ROOT 4 [hp_X]/20 mL
INACTIVE INGREDIENTS: ALCOHOL; WATER

Unda 44

Active ingredients
Each drop contains:
Argentum metallicum (Silver) 12X
Aurum metallicum (Gold) 12X
Cytisus scoparius (Scotch broom) Aerial Parts 4X
Dulcamara (Bittersweet) Shoots 4X
Inula helenium (Elecampane) Root 4X
Juniperus communis (Common juniper) Berry 4X
Stigmata maidis (Maize) Style and Stigma 4X
Uva-ursi (Bearberry) Leaf 4X

Uses
For the temporary relief of symptoms
associated with minor urinary discomfort.

Warnings
Stop use and ask a doctor if symptoms persist or worsen.

If pregnant or breastfeeding, ask a health professional before use.
Keep out of reach of children. In case of overdose, get medical help or contact
a Poison Control Center right away.

PREGNANCY OR BREAST FEEDING

If pregnant or breastfeeding, ask a health professional before use.

Keep out of reach of children.

OVERDOSAGE

In case of overdose, get medical help or contact a

Poison Control Center right away.

Stop use and ask a doctor if symptoms persist or worsen.

Other information
Do not use if seal is missing or broken.
Store in a cool, dry place.

Inactive Ingredients:

Ethanol (beet),
purified water

Directions:

Adults and adolescents (12 years and older)

Take 5 drops three times daily or as recommended by your healthcare practitioner.

Children (under 12 years)

Take under the direction of your healthcare practitioner.

Uses
For the temporary relief of symptoms associated with minor urinary discomfort.

Directions:

Adults and adolescents (12 years and older)

Take 5 drops three times daily or as recommended by your healthcare practitioner.

Children (under 12 years)

Take under the direction of your healthcare practitioner.

PACKAGE LABEL

NDC 62106-1143-8

UNDA

numbered compounds

UNDA 44

Homeopathic Preparation

For the temporary
relief of symptoms
associated with minor
urinary discomfort.

Contains 31% Alcohol
0.7 fl oz (20 ml)